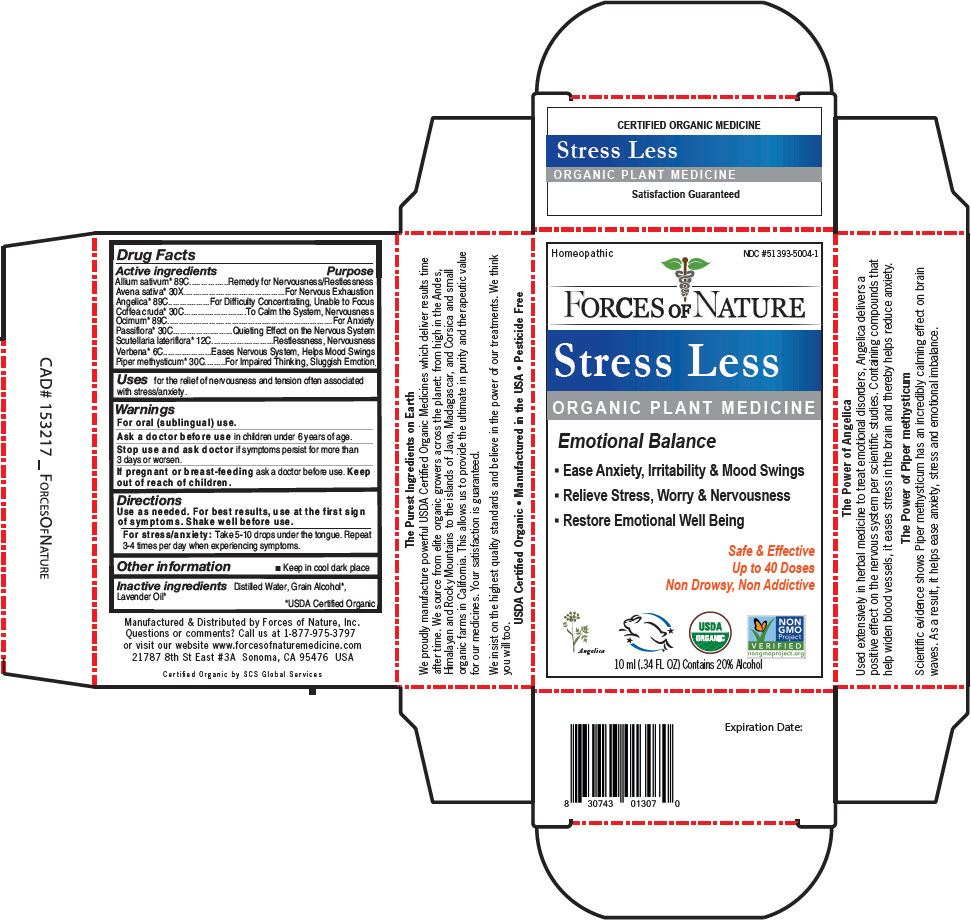 DRUG LABEL: Stress Less
NDC: 51393-5004 | Form: SOLUTION/ DROPS
Manufacturer: Forces of Nature
Category: homeopathic | Type: HUMAN OTC DRUG LABEL
Date: 20200421

ACTIVE INGREDIENTS: Garlic 89 [hp_C]/100 mL; Avena Sativa Top 30 [hp_X]/100 mL; Angelica Archangelica Root 89 [hp_C]/100 mL; Arabica Coffee Bean 30 [hp_C]/100 mL; Holy Basil Leaf 89 [hp_C]/100 mL; Passiflora Edulis Flower 30 [hp_C]/100 mL; Scutellaria Lateriflora 12 [hp_C]/100 mL; Verbena Hastata Top 6 [hp_C]/100 mL; Macropiper Methysticum Root 30 [hp_C]/100 mL
INACTIVE INGREDIENTS: Water; Alcohol; Lavender Oil

Stress Less

Drug Facts

ACTIVE INGREDIENT

Active ingredients | Purpose
Allium sativum [USDA Certified Organic] 89C | Remedy for Nervousness/Restlessness
Avena sativa 30X | For Nervous Exhaustion
Angelica 89C | For Difficulty Concentrating, Unable to Focus
Coffea cruda 30C | To Calm the System, Nervousness
Ocimum 89C | For Anxiety
Passiflora 30C | Quieting Effect on the Nervous System
Scutellaria lateriflora 12C | Restlessness, Nervousness
Verbena 6C | Eases Nervous System, Helps Mood Swings
Piper methysticum 30C | For Impaired Thinking, Sluggish Emotion

Uses

for the relief of nervousness and tension often associated with stress/anxiety.

Warnings

For oral (sublingual) use.

Ask a doctor before use in children under 6 years of age.

Stop use and ask doctor if symptoms persist for more than 3 days or worsen.

PREGNANCY OR BREAST FEEDING

If pregnant or breast-feeding ask a doctor before use.

Keep out of reach of children.

Directions

Use as needed. For best results, use at the first sign of symptoms. Shake well before use.

For stress/anxiety

Take 5-10 drops under the tongue. Repeat 3-4 times per day when experiencing symptoms.

Other information

- Keep in cool dark place

Inactive ingredients

Distilled Water, Grain Alcohol, Lavender Oil

Questions or comments?

Call us at 1-877-975-3797 or visit our website www.forcesofnaturemedicine.com

Manufactured & Distributed by Forces of Nature, Inc.
21787 8th St East # 3A Sonoma, CA 95476 USA

PRINCIPAL DISPLAY PANEL - 10 ml Bottle Carton

Homeopathic
NDC #51393-5004-1

FORCES OF NATURE

Stress Less
ORGANIC PLANT MEDICINE

Emotional Balance

- Ease Anxiety, Irritability & Mood Swings
- Relieve Stress, Worry & Nervousness
- Restore Emotional Well Being

Safe & Effective
Up to 40 Doses
Non Drowsy, Non Addictive

Angelica

USDA
ORGANIC

NON
GMO
Project
VERIFIED
nongmoproject.org

10 ml (.34 FL OZ) Contains 20% Alcohol